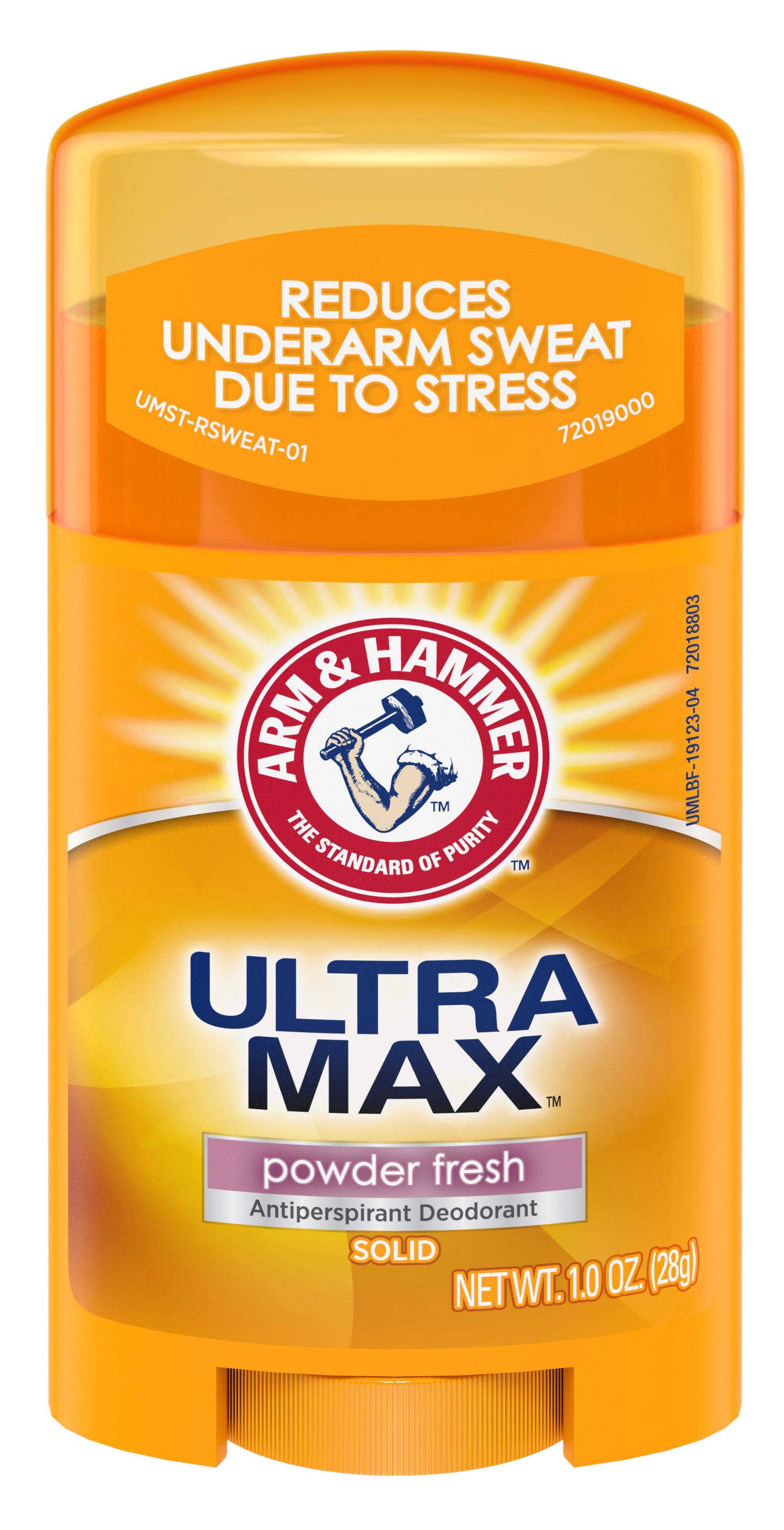 DRUG LABEL: UltraMax Invisible Solid - Powder Fresh
NDC: 10237-870 | Form: STICK
Manufacturer: Church & Dwight Co., Inc.
Category: otc | Type: HUMAN OTC DRUG LABEL
Date: 20241120

ACTIVE INGREDIENTS: ALUMINUM CHLOROHYDRATE 0.19 g/1 g
INACTIVE INGREDIENTS: C12-20 ALKYL BENZOATE; PETROLATUM; XANTHAN GUM; CYCLOMETHICONE 5; STEARYL ALCOHOL; PPG-14 BUTYL ETHER; TALC; HYDROGENATED CASTOR OIL; SODIUM BICARBONATE; STARCH, CORN; MALTODEXTRIN

Arm and Hammer UltraMax Invisible Solid - Powder Fresh Scent

ACTIVE INGREDIENT

Aluminum Chlorohydrate 19%

PURPOSE

Antiperspirant

INDICATIONS AND USAGE

Usereduces underarm perspiration

WARNINGS

For external use only

Do not useon broken skin

Stop use ifrash or irritation occurs

Ask a doctor before use if you havekidney disease

Keep out of reach of children.If swallowed, get medical help or contact a Poison Control Center right away.

Directions

Apply a thin layer to underarms only

INACTIVE INGREDIENT

PPG-14 Butyl Ether, Cyclopentasiloxane, Stearyl Alcohol, C12-15 Alkyl Benzoate, Talc, Hydrogenated Castor Oil, Petrolatum, Fragrance, Sodium Bicarbonate (Baking Soda), Corn Starch Modified, Polysaccharides, Maltodextrin

Questions or Comments?

Call 1-800-248-8820

M-F 9am-5pm ET

or visit www.ahultramax.com

PACKAGE LABEL

REDUCES

UNDERARM SWEAT

DUE TO STRESS

Arm and Hammer

THE STANDARD OF PURITY

ULTRA MAX

powder fresh

Antiperspirant Deodorant

SOLID

NET WT. 1.0 OZ. (28g)